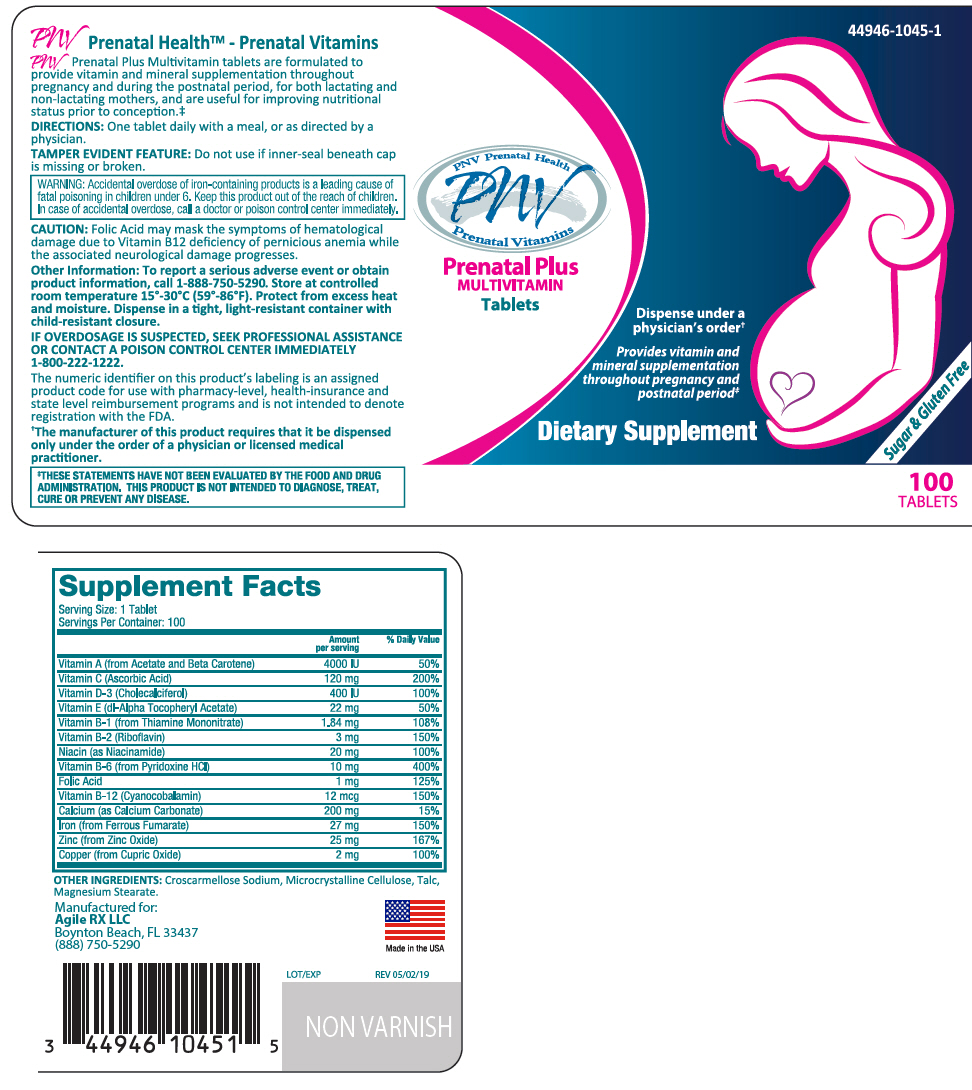 DRUG LABEL: PNV Prenatal Plus Multivitamin
NDC: 44946-1045 | Form: TABLET
Manufacturer: Agile RX
Category: other | Type: DIETARY SUPPLEMENT
Date: 20231107

ACTIVE INGREDIENTS: VITAMIN A ACETATE 2000 [iU]/1 1; BETA CAROTENE 2000 [iU]/1 1; ASCORBIC ACID 120 mg/1 1; CHOLECALCIFEROL 400 [iU]/1 1; .ALPHA.-TOCOPHEROL ACETATE, DL- 22 mg/1 1; THIAMINE MONONITRATE 1.84 mg/1 1; RIBOFLAVIN 3 mg/1 1; NIACINAMIDE 20 mg/1 1; PYRIDOXINE HYDROCHLORIDE 10 mg/1 1; FOLIC ACID 1 mg/1 1; CYANOCOBALAMIN 12 ug/1 1; CALCIUM CARBONATE 200 mg/1 1; FERROUS FUMARATE 27 mg/1 1; ZINC OXIDE 25 mg/1 1; CUPRIC OXIDE 2 mg/1 1
INACTIVE INGREDIENTS: CROSCARMELLOSE SODIUM; MICROCRYSTALLINE CELLULOSE; TALC; MAGNESIUM STEARATE

PNV Prenatal Plus MULTIVITAMIN Tablets

STATEMENT OF IDENTITY

Supplement Facts
Serving Size: 1 Tablet
Servings Per Container: 100
 | Amount per serving | % Daily Value
Vitamin A (from Acetate and Beta Carotene) | 4000 IU | 50%
Vitamin C (Ascorbic Acid) | 120 mg | 200%
Vitamin D-3 (Cholecalciferol) | 400 IU | 100%
Vitamin E (dl-Alpha Tocopheryl Acetate) | 22 mg | 50%
Vitamin B-1 (from Thiamine Mononitrate) | 1.84 mg | 108%
Vitamin B-2 (Riboflavin) | 3 mg | 150%
Niacin (as Niacinamide) | 20 mg | 100%
Vitamin B-6 (from Pyridoxine HCl) | 10 mg | 400%
Folic Acid | 1 mg | 125%
Vitamin B-12 (Cyanocobalamin) | 12 mcg | 150%
Calcium (as Calcium Carbonate) | 200 mg | 15%
Iron (from Ferrous Fumarate) | 27 mg | 150%
Zinc (from Zinc Oxide) | 25 mg | 167%
Copper (from Cupric Oxide) | 2 mg | 100%

OTHER INGREDIENTS: Croscarmellose Sodium, Microcrystalline Cellulose, Talc, Magnesium Stearate.

HEALTH CLAIM

PNV Prenatal Plus Multivitamin tablets are formulated to provide vitamin and mineral supplementation throughout pregnancy and during the postnatal period, for both lactating and non-lactating mothers, and are useful for improving nutritional status prior to conception.‡

DIRECTIONS

One tablet daily with a meal, or as directed by a physician.

TAMPER EVIDENT FEATURE

Do not use if inner-seal beneath cap is missing or broken.

WARNINGS

WARNING: Accidental overdose of iron-containing products is a leading cause of fatal poisoning in children under 6. Keep this product out of the reach of children. In case of accidental overdose, call a doctor or poison control center immediately.

CAUTION

Folic Acid may mask the symptoms of hematological damage due to Vitamin B12 deficiency of pernicious anemia while the associated neurological damage progresses.

Other Information

To report a serious adverse event or obtain product information, call 1-888-750-5290. Store at controlled room temperature 15°-30°C (59°-86°F). Protect from excess heat and moisture. Dispense in a tight, light-resistant container with child-resistant closure.

SAFE HANDLING WARNING

IF OVERDOSAGE IS SUSPECTED, SEEK PROFESSIONAL ASSISTANCE OR CONTACT A POISON CONTROL CENTER IMMEDIATELY 1-800-222-1222.

HEALTH CLAIM

The numeric identifier on this product's labeling is an assigned product code for use with pharmacy-level, health-insurance and state level reimbursement programs and is not intended to denote registration with the FDA.

†The manufacturer of this product requires that it be dispensed only under the order of a physician or licensed medical practitioner.

‡THESE STATEMENTS HAVE NOT BEEN EVALUATED BY THE FOOD AND DRUG ADMINISTRATION. THIS PRODUCT IS NOT INTENDED TO DIAGNOSE, TREAT, CURE OR PREVENT ANY DISEASE.

HEALTH CLAIM

Manufactured for:
Agile RX LLC
Boynton Beach, FL 33437
(888) 750-5290

Made in the USA

LOT/EXP
REV 05/02/19

PRINCIPAL DISPLAY PANEL - 100 Tablet Bottle Label

44946-1045-1

PNV Prenatal Health
PNV
Prenatal Vitamins

Prenatal Plus
MULTIVITAMIN
Tablets

Dispense under a
physician's order†

Provides vitamin and
mineral supplementation
throughout pregnancy and
postnatal period‡

Dietary Supplement

Sugar & Gluten Free

100
TABLETS